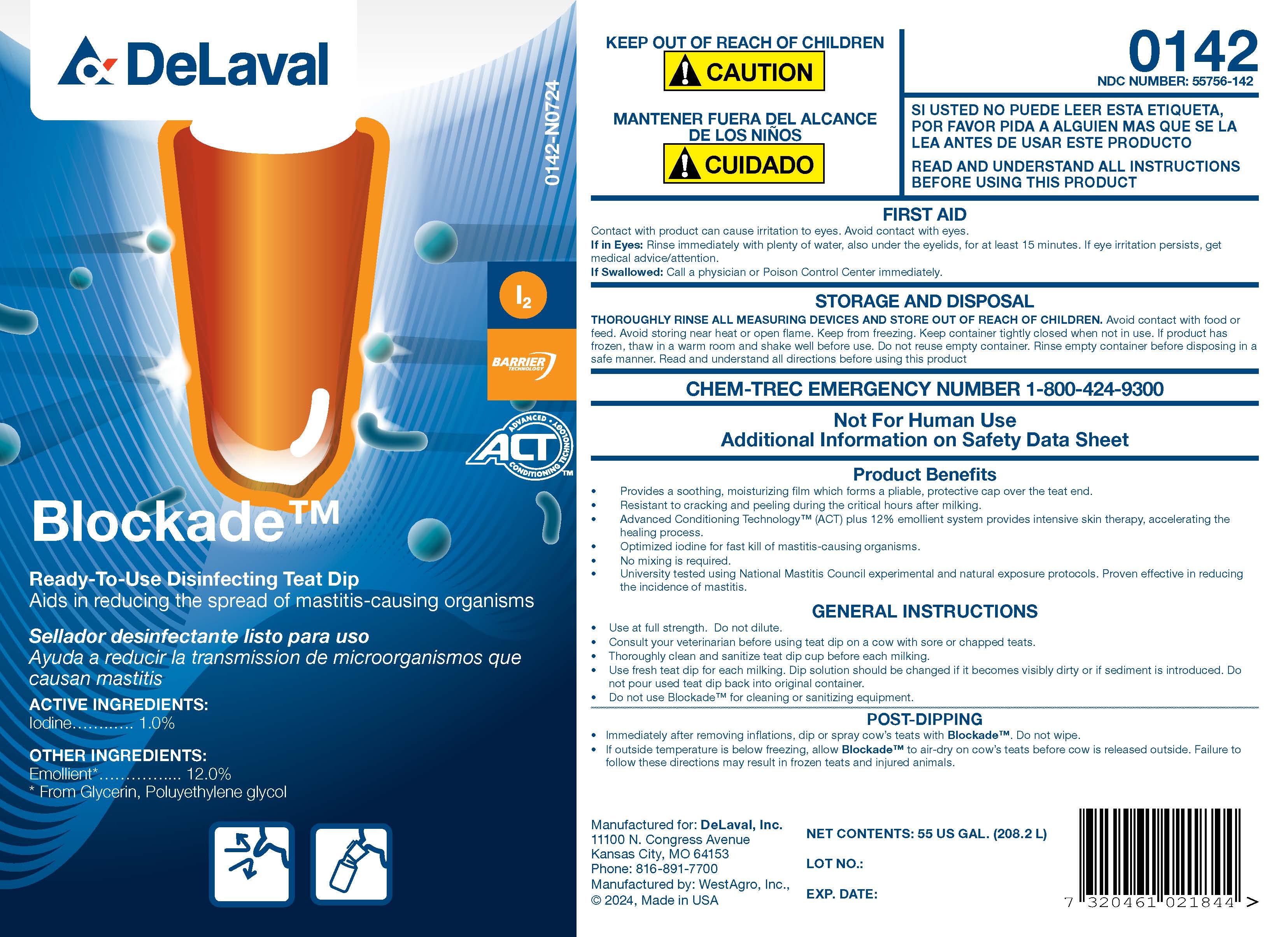 DRUG LABEL: Blockade
NDC: 55756-142 | Form: SOLUTION
Manufacturer: DeLaval, Inc.
Category: animal | Type: OTC ANIMAL DRUG LABEL
Date: 20241122

ACTIVE INGREDIENTS: IODINE 10.4 g/1 L
INACTIVE INGREDIENTS: SODIUM HYDROXIDE; ANHYDROUS CITRIC ACID; GLYCERIN; POLOXAMER 403; POLOXAMER 335; SODIUM CHLORIDE; XANTHAN GUM; POVIDONE K30; SODIUM IODIDE; POLYETHYLENE GLYCOL 400; DOCUSATE SODIUM; ALLANTOIN; SODIUM IODATE; WATER

BLOCKADE

PURPOSE

Ready-To-Use Disinfecting Teat Dip

Aids in reducing the spread of mastitis-causing organisms

ACTIVE INGREDIENTS:
Iodine ............................................... 1.0%

INACTIVE INGREDIENT

OTHER INGREDIENTS:

Emollient*...............12.0%

* From Glycerin, Poluyethylene glycol

Product Benefits

- Provides a soothing, moisturizing film which forms a pliable, protective cap over the teat end.
- Resistant to cracking and peeling during the critical hours after milking.
- Advanced Conditioning Technology™(ACT) plus 12% emollient system provides intensive skin therapy, accelerating the healing process.
- Optimized iodine for fast kill of mastitis-causing organisms.
- No mixing is required.
- University tested using National Mastitis Council experimental and natural exposure protocols. Proven effective in reducing the incidence of mastitis.

INDICATIONS AND USAGE

GENERAL INSTRUCTIONS

- Use at full strength. Do not dilute.
- Consult your veterinarian before using teat dip on a cow with sore or chapped teats.
- Thoroughly clean and sanitize teat dip cup before each milking.
- Use fresh teat dip for each milking. Dip solution should be changed if it becomes visibly dirty or if sediment is introduced. Do not pour used teat dip back into original container.
- Do not use Blockade for cleaning or sanitizing equipment.

POST-DIPPING

- Immediately after removing inflations, dip or spray cow's teats with Blockade™. Do not wipe.
- If outside temperature is below freezing, allow Blockade™ to air-dry on cow's teats before cow is released outside. Failure to follow these directions may result in frozen teats and injured animals.

Manufactured for: DeLaval, Inc.

11100 N. Congress Avenue

Kansas City, MO 64153

Phone: 816-891-7700

Manufactured by: WestAgro, Inc.,

© 2024, Made in USA

KEEP OUT OF REACH OF CHILDREN

! CAUTION

MANTENER FUERA DEL ALCANCE DE LOS NINOS

! CUIDADO

READ AND UNDERSTAND ALL INSTRUCTIONS BEFORE USING THIS PRODUCT

FIRST AID

Contact with product can cause irritation to eyes. Avoid contact with eyes.

If in Eyes: Rinse immdiately with plenty of water, also under eyelids, for at least 15 minutes. If eye irritation peersists, get medical advice/attention.

If Swallowed: Call a physician or Poison Control Center immediately.

Not For Human Use

Additional Information on Safety Data Sheet

STORAGE AND DISPOSAL

THOROUGHLY RINSE ALL MEASURING DEVICES AND STORE OUT OF REACH OF CHILDREN. Avoid contact with food or feed. Avoid storing near heat or open flame. Keep from freezing. Keep container tightly closed when not in use. If product has frozen, thaw in a warm room and shake well before use. Do not reuse empty container. Rinse empty container before disposing in a safe manner. Read and understand all directions before using this product

CHEM-TREC EMERGENCY NUMBER 1-800-424-9300

NET CONTENTS:

LOT NO.:

EXPIRATION DATE:

PACKAGE LABEL

Add image transcription here...